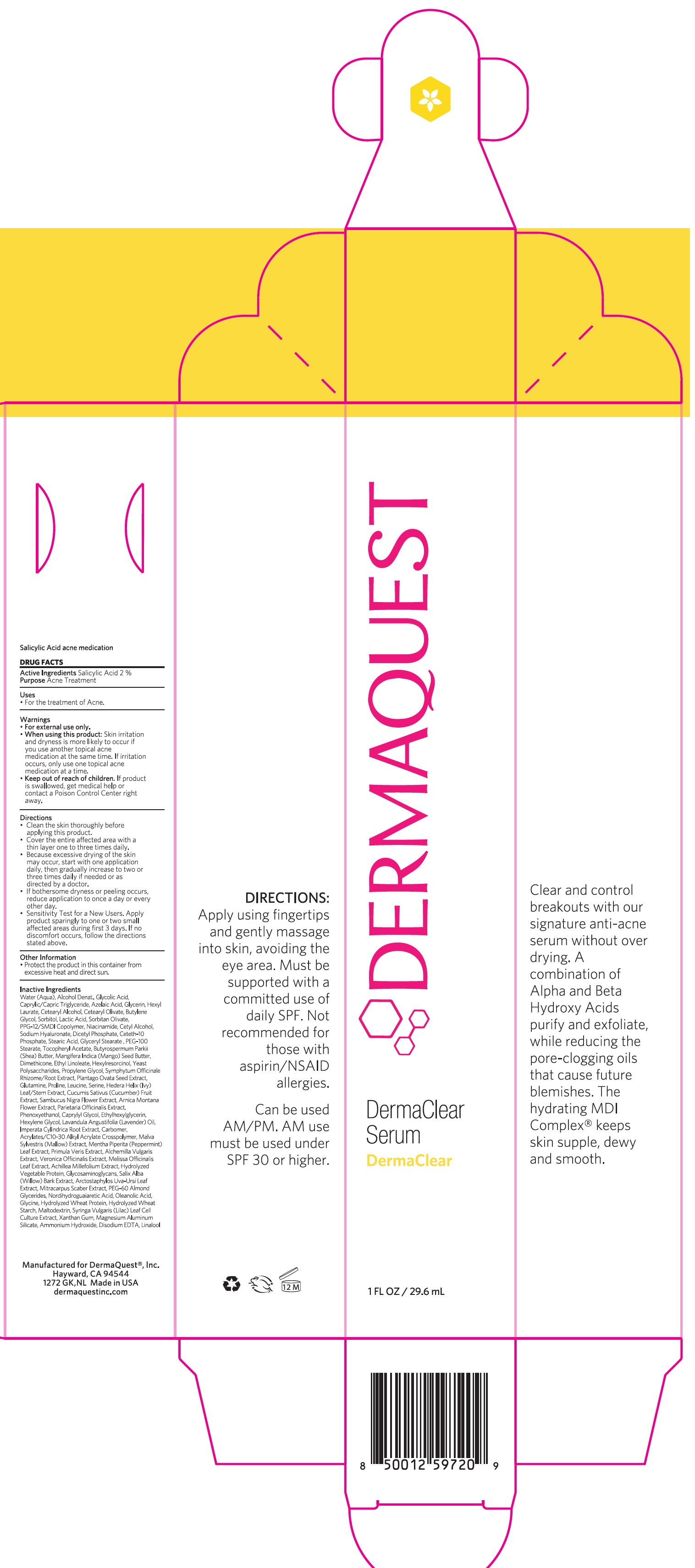 DRUG LABEL: DermaClear Serum
NDC: 62742-4069 | Form: CREAM
Manufacturer: Allure Labs Inc
Category: otc | Type: HUMAN OTC DRUG LABEL
Date: 20241204

ACTIVE INGREDIENTS: SALICYLIC ACID 20 mg/1 mL
INACTIVE INGREDIENTS: LACTIC ACID, UNSPECIFIED FORM; NIACINAMIDE; DIMETHICONE; YEAST; PROLINE; WATER; ALCOHOL; MEDIUM-CHAIN TRIGLYCERIDES; GLYCERIN; BUTYLENE GLYCOL; SORBITOL; CETYL ALCOHOL; HYALURONATE SODIUM; CETETH-10 PHOSPHATE; PROPYLENE GLYCOL; GLUTAMINE; LEUCINE; SERINE; HEDERA HELIX LEAF; SAMBUCUS NIGRA FLOWER; IMPERATA CYLINDRICA ROOT; MALVA SYLVESTRIS FLOWERING TOP; MENTHA PIPERITA LEAF; ALCHEMILLA XANTHOCHLORA FLOWERING TOP; ARNICA MONTANA FLOWER; PARIETARIA OFFICINALIS LEAF; PHENOXYETHANOL; ETHYLHEXYLGLYCERIN; LAVENDER OIL; CARBOMER COPOLYMER TYPE A; PRIMULA VERIS; ACHILLEA MILLEFOLIUM; CETOSTEARYL ALCOHOL; SORBITAN OLIVATE; MANGIFERA INDICA SEED BUTTER; HEXYLRESORCINOL; COMFREY ROOT; HEXYLENE GLYCOL; VERONICA OFFICINALIS FLOWERING TOP; MELISSA OFFICINALIS LEAF; GAG; SALIX ALBA BARK; OLEANOLIC ACID; CETEARYL OLIVATE; PPG-12/SMDI COPOLYMER; DIHEXADECYL PHOSPHATE; STEARIC ACID; GLYCERYL MONOSTEARATE; ARCTOSTAPHYLOS UVA-URSI LEAF; PEG-60 ALMOND GLYCERIDES; NORDIHYDROGUAIARETIC ACID, (+/-)-; PEG-100 STEARATE; MITRACARPUS HIRTUS WHOLE; HYDROLYZED WHEAT PROTEIN (ENZYMATIC, 3000 MW); MALTODEXTRIN; SYRINGA VULGARIS WHOLE; XANTHAN GUM; MAGNESIUM ALUMINUM SILICATE; AMMONIA; EDETATE DISODIUM; GLYCOLIC ACID; AZELAIC ACID; HEXYL LAURATE; ALPHA-TOCOPHEROL ACETATE; SHEA BUTTER; ETHYL LINOLEATE; PLANTAGO OVATA SEED; CUCUMBER; CAPRYLYL GLYCOL; LINALOOL, (+/-)-

Drug Facts

Active Ingredients: Salicylic Acid 2%

Purpose: Acne Treatment

Uses:

For the treatment of acne

Warnings:

For external use only.

When Using this product: Skin irritation and dryness is more likely to occur if you use another topical acne medication at the same time.

STOP USE

If irritation occurs, only use one topical acne medication at a time.

Keep out of reach of children.

If product is swallowed, get medical help or contact a Poison Control Center right away.

Directions

- Clean the skin thoroughly before before applying this product.
- Cover the entire affected area with a thin layer one to three times daily.
- Because excessive drying of the skin may occur, stsart with one application daily, then gradually increase to two or three times daily if needed or as directed vy doctor.
- If bothersome dryness or peeling occurs, reduce applicaiton to ince a day or every other day.
- Sensitivity Test for a new users. Apply product sparingly to one or two small affected areas during first 3 days. If no discomfort occurs, follwo the directions atated above.

Other Information:

Protect the product in this container from the excessive heat and direct sun.

INACTIVE INGREDIENT

Water (Aqua), Alcohol Denat., Glycolic Acid, Caprylic / Capric Triglyceride, Azelaic Acid, Glycerin, Hexyl Laurate, Cetearyl Alcohol, Cetearyl Olivate, Butylene Glycol, Sorbitol, Lactic Acid, Sorbitan Olivate, PPG-12 /SMDI Copolymer, Niacinamide, Cetyl Alcohol, Sodium Hyaluronate, Dicetyl Phosphate, Ceteth-10 Phosphate, Srearic Acid, Glyceryl Stearate, PEG-100 Stearate, Tocopheryl Acetate, Butyrospermum Parkii (Shea) Butter, Mangifera Indiaca (Mango) Seed Butter, Dimethicone, Ethyl Linoleate, Hexylrsorcinol, Yeast Ploysaccharides, Propylene Glycol, Symphytum Officinales Rhizome/Root Extract, Plantago Ovata Seed Extract, Glutamine, Proline, Leucine, Serine, Hedera, Helix (Ivy) Leaf/Stem Extract, Cucumis Sativus Fruit Extract, Sambucus Nigra Flower Extract, Arnica Montana Flower Extract, Parietaria Officinalis Extract, Phenoxyethanol, Caprylyl Glycol, Ethylhexylglycerine, Hexylene Glycol, Lavandula Angustifoia (Lavender) Oil, Imperata Cylindrica (Root) Extract, Carbomer, Acrylates/C10-30 Alkyl Acrylate Crosspolymer, Malva Sylvestris (Mallow) Extract, Mentha Piperita (Peppermint) Leaf Extract, Primula Veris Extract, Alchemilla Vulgaris Extract, Veronica Officinalis Extract, Melissa Officinalis Leaf Extract, Achillea Mellifolium Extract, Hydrolyzed Vegetable Protein, Glycosaminoglycans, Salix Alba (Willlow) Bark Extract, Arcaptostaphylos, Uva Ursi Leaf Extract, Mitracarpus Scaber Extract, PEG-60 Almond Glycerides, Nordihydroguaiaretic Acid, Oleanolic Acid. Glycerin, Hydrolyzed wheat Protein, Hydrolyzed Wheat Starch, Maltodextrin, Syringa Vulgaris (Lilac) Leaf Cell Culture Extract, Xanthan Gum, Magnesium Aluminum Silicate, Ammonium Hydroxide, Disodium EDTA, Linalool

PACKAGE LABEL

Manufactured for Dermaquest Inc
Hayward, CA 94544
1272 GK, NL Made in USA
dermaquestinc.com